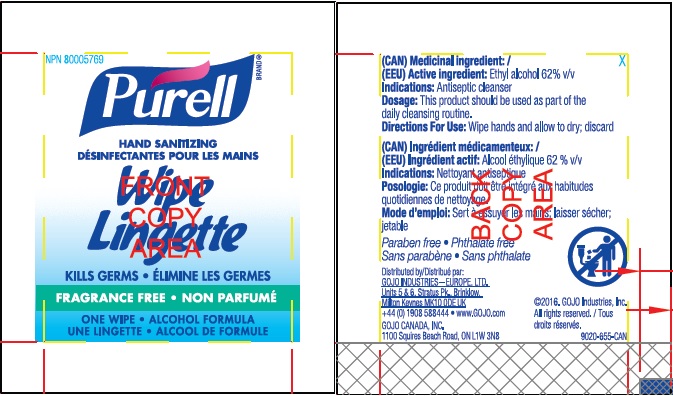 DRUG LABEL: PURELL Hand Sanitizing Wipe Alcohol Formula
NDC: 21749-301 | Form: CLOTH
Manufacturer: GOJO Industries, Inc.
Category: otc | Type: HUMAN OTC DRUG LABEL
Date: 20241231

ACTIVE INGREDIENTS: ALCOHOL 62 mL/100 mL
INACTIVE INGREDIENTS: WATER; ISOPROPYL ALCOHOL; GLYCERIN; ISOPROPYL MYRISTATE; PROPYLENE GLYCOL; VITAMIN A PALMITATE; .ALPHA.-TOCOPHEROL ACETATE; CORN OIL

PURELL Hand Sanitizing Wipe Alcohol Formula